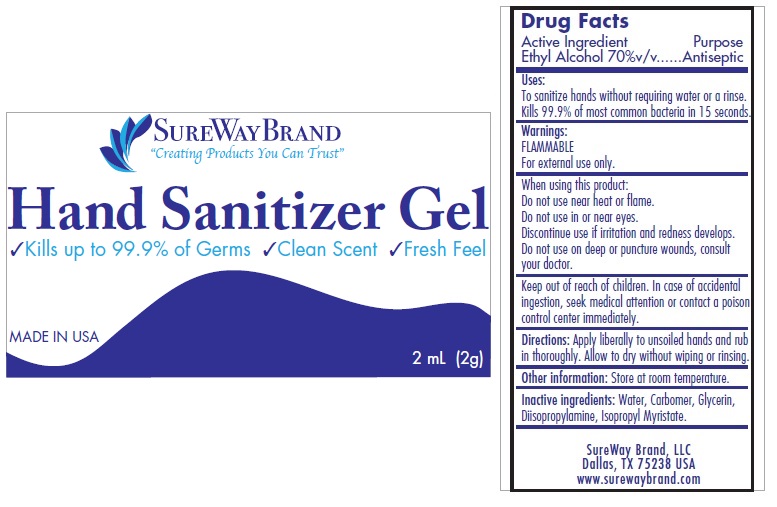 DRUG LABEL: SureWay brand Hand Sanitizer Gel
NDC: 81152-070 | Form: GEL
Manufacturer: Sureway Brand Llc
Category: otc | Type: HUMAN OTC DRUG LABEL
Date: 20210104

ACTIVE INGREDIENTS: ALCOHOL 0.70 mL/1 mL
INACTIVE INGREDIENTS: WATER; CARBOMER HOMOPOLYMER, UNSPECIFIED TYPE; GLYCERIN; DIISOPROPYLAMINE; ISOPROPYL MYRISTATE

SureWay brand Hand Sanitizer Gel

Active Ingredient

Ethyl Alcohol 70%v/v

Purpose

Antiseptic

Uses:

To sanitize hands without requiring water or a rinse.
Kills 99.9% of most common bacteria in 15 seconds.

Warnings:

FLAMMABLE

For external use only.

When using this product:

Do not use near heat or flame.

Do not use in or near eyes.

Discontinue use if irritation and redness develops.

Do not use on deep or puncture wounds, consult your doctor.

Keep out of reach of children. In case of accidental ingestion, seek medical attention or contact a poison control center immediately.

Directions:

Apply liberally to unsoiled hands and rub in thoroughly. Allow to dry without wiping or rinsing.

Other information:

Store at room temperature.

Inactive ingredients:

Water, Carbomer, Glycerin, Diisoproplylamine, Isopropyl Myristate.

“Creating Products You Can Trust”

√Kills up to 99.9% of Germs √Clean Scent √Fresh Feel

MADE IN USA
SureWay Brand, LLC
Dallas, TX 75238 USA
www.surewaybrand.com